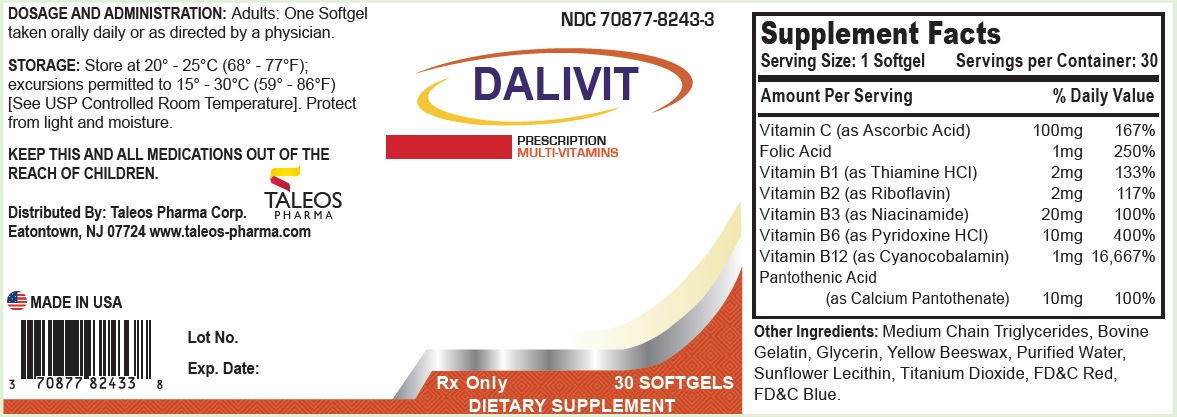 DRUG LABEL: DALIVIT
NDC: 70877-8243 | Form: CAPSULE, COATED
Manufacturer: Taleos Pharma
Category: other | Type: DIETARY SUPPLEMENT
Date: 20180406

ACTIVE INGREDIENTS: ASCORBIC ACID 100 mg/1 1; FOLIC ACID 1 mg/1 1; THIAMINE HYDROCHLORIDE 2 mg/1 1; RIBOFLAVIN 2 mg/1 1; NIACINAMIDE 20 mg/1 1; PYRIDOXINE HYDROCHLORIDE 10 mg/1 1; CYANOCOBALAMIN 1 mg/1 1; CALCIUM PANTOTHENATE 10 mg/1 1
INACTIVE INGREDIENTS: MEDIUM-CHAIN TRIGLYCERIDES; GLYCERIN; YELLOW WAX; WATER; LECITHIN, SUNFLOWER; TITANIUM DIOXIDE

DALIVIT Softgels

HEALTH CLAIM

Rx Only

DESCRIPTION

DAIVIT is a prescription multi-vitamin in the form of a red, oval, softgel.

INDICATION AND USAGE

DALIVIT is a prescription multi-vitamin supplement that can be taken to improve nutritional status in conditions requiring dietary supplementation. DALIVIT can also be used for the dietary management of individuals with distinct nutritional needs under a physician or healthcare provider’s supervision for end stage failure, dialysis, hyperhomocysteinemia or inadequate dietary vitamin intake.

CONTRAINDICATIONS

This product is contraindicated in patients with a known hypersensitivity to any of the ingredients.

WARNING

Folic Acid in doses above 0.1 mg daily may obscure pernicious anemia in that hematological remission can occur while neurological manifestations remain progressive. Folic Acid alone is improper therapy in the treatment of pernicious anemia and other megaloblastic anemias where vitamin B12 is deficient.

DO NOT EXCEED RECOMMENDED DOSAGE.

KEEP THIS AND ALL MEDICATIONS OUT OF THE REACH OF CHILDREN.

PRECAUTIONS

Folic Acid in doses above 0.1 mg daily may obscure pernicious anemia in that hematological remission can occur while neurological manifestations remain progressive. The 1 mg of cyanocobalamin contained in DALIVIT Softgels has been shown to provide an adequate amount of cyanocobalamin to address this precaution. A safer upper limit of 100 mg per day has been established for the unsupervised medical use of pyridoxine. Consider all sources of pyridoxine supplementation when prescribing DALIVIT Softgels.

If pregnant, or planning to become pregnant or are currently breast-feeding please contact your physician, or healthcare provider before using or continuing use of this medication.

ADVERSE REACTIONS

Allergic sensitization has been reported following both oral and parenteral administration of folic acid. Paresthesia and somnolence have been reported with the use of pyridoxine hydrochloride. Mild transient diarrhea, polycynthemia vera, peripheral vascular thrombosis, itching transitory exanthema and feeling of swelling of the entire body has been associated with the use of cyanocobalamin.

DRUG INTERACTIONS

Pyridoxine supplements should not be given to patients receiving the drug levodopa, because the action of levodopa is antagonized by pyridoxine. However, pyridoxine may be used concurrently in patients receiving a preparation containing both carbidopa and levodopa. Concurrent use of phenytoin and folacin (folic acid) may result in decreased phenytoin effectiveness.

DOSAGE AND ADMINISTRATION

Adults: One Softgel taken orally daily or as directed by a physician.

DO NOT EXCEED RECOMMENDED DOSAGE.

STATEMENT OF IDENTITY

Supplement Facts
Serving Size: 1 Softgel | Servings per Container: 30
Amount Per Serving | % Daily Value
Vitamin C (as Ascorbic Acid) | 100mg | 167%
Folic Acid | 1mg | 250%
Vitamin B1 (as Thiamine HCl) | 2mg | 133%
Vitamin B2 (as Riboflavin) | 2mg | 117%
Vitamin B3 (as Niacinamide) | 20mg | 100%
Vitamin B6 (as Pyridoxine HCl) | 10mg | 400%
Vitamin B12 (as Cyanocobalamin) | 1mg | 16,667%
Pantothenic Acid (as Calcium Pantothenate) | 10mg | 100%

STORAGE

Store at 20° - 25°C (68° - 77°F); excursions permitted to 15° - 30°C (59° - 86°F) [See USP Controlled Room Temperature.]

Protect from light and moisture.
Dispense in a well-closed, tight, light-resistant container as defined by the USP using a child resistant closure.

HOW SUPPLIED

DALIVIT softgels are supplied as red softgel. DALIVIT softgels are available in bottles of 30 (70877-8243-3). Each softgel of Dalivit contains 100 mg ascorbic acid, 1 mg of Folic Acid, 2 mg of thiamine hydrochloride, 2 mg of riboflavin, 20 mg of niacinamide, 10 mg of pyridoxine hydrochloride, 1 mg of cyanocobalamin, and 10 mg of calcium pantothenate.

Distributed By:
Taleos Pharma Corp.
Eatontown, NJ 07724
www.taleos-pharma.com

PRINCIPAL DISPLAY PANEL - 30 Softgel Bottle Label

70877-8243-3

DALIVIT

PRESCRIPTION
MULTI-VITAMINS

Rx Only 30 SOFTGELS

DIETARY SUPPLEMENT